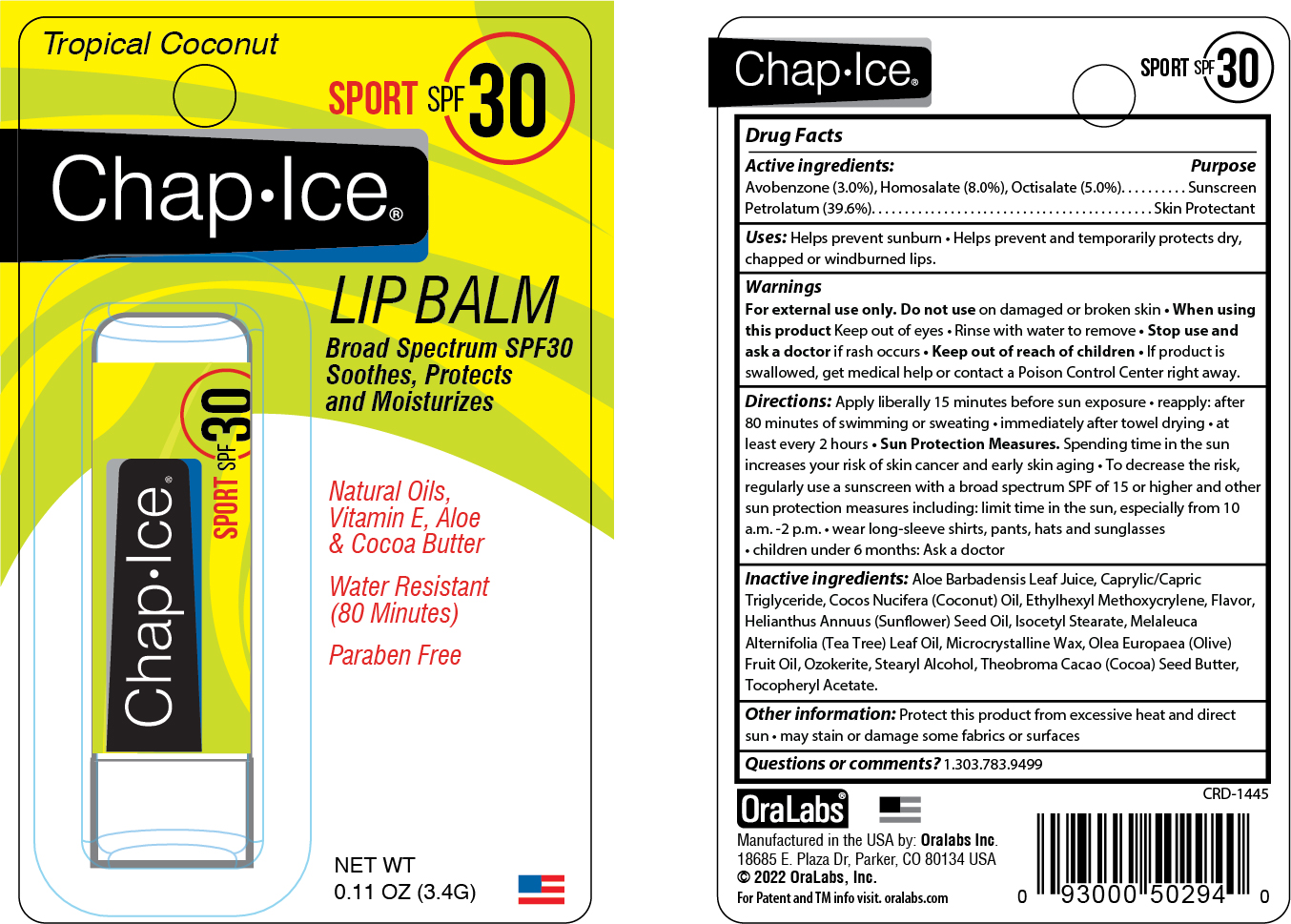 DRUG LABEL: ChapIce SPF 30 Lip Balm
NDC: 63645-180 | Form: STICK
Manufacturer: OraLabs
Category: otc | Type: HUMAN OTC DRUG LABEL
Date: 20250422

ACTIVE INGREDIENTS: OCTISALATE 50 mg/1 g; AVOBENZONE 30 mg/1 g; PETROLATUM 396 mg/1 g; HOMOSALATE 80 mg/1 g
INACTIVE INGREDIENTS: CERESIN 165 mg/1 g; ISOCETYL STEARATE 23 mg/1 g; .ALPHA.-TOCOPHEROL ACETATE 5 mg/1 g

Drug Facts

Active ingredient

Avobenzone (3.0%), Octisalate (5.0%), Homosalate (8.0%)

Petrolatum (39.6%)

Purpose

Sunscreen, Sunscreen, Skin Protectant

Keep Out of Reach of Children

If swallowed get medical help or contact a Poison Control Center right away.

Uses

Helps prevent sunburn. if used as directed with other sun protection measures (see Directions) decreases the risk of skin cancer and early aging caused by the sun. helps prevent and temporarily protects chafed, chapped or cracked lips. Helps prevent and protect from the drying effects of wind and cold weather

Warnings

For external use only: Do not use on damaged or broken skin. When using this product. Keep out of eyes. Rinse with water to remove. Stop use and ask a doctor: if rash occurs

Directions

Apply liberally 15 minutes before sun exposure. Reapply: after 80 minutes of swimming or sweating. Immediately after towel drying. At least every 2 hours. SunProtectionMeasures. Spending time in the sun increases your risk of skin cancer and early skin aging. To decrease the risk, regularly use a sunscreen with a broad spectrum SPF of 15 or higher and other sun protection measures including: limit time in the sun, especially from 10 a.m. to 2 p.m. wear long-sleeve shirts, pants, hats and sunglasses. Children under 6 months: Ask a doctor.

Inactive Ingredients

Aloe Barbadensis Leaf Extract, Beeswax, Caprylic/Capric Triglyceride, Cocos Nucifera (Coconut) Oil, Ethylhexyl Methoxycrylene, Flavor, Helianthus Annuus (Sunflower) Seed Oil, Isocetyl Stearate, Melaleuca Alternifolia (Tea Tree) Leaf Oil, Microcrystalline Wax, Olea Europaea (Olive) Fruit Oil, Ozokerite, Stearyl Alcohol, Theobroma Cacao (Cocoa) Seed Butter, Tocopheryl Acetate.